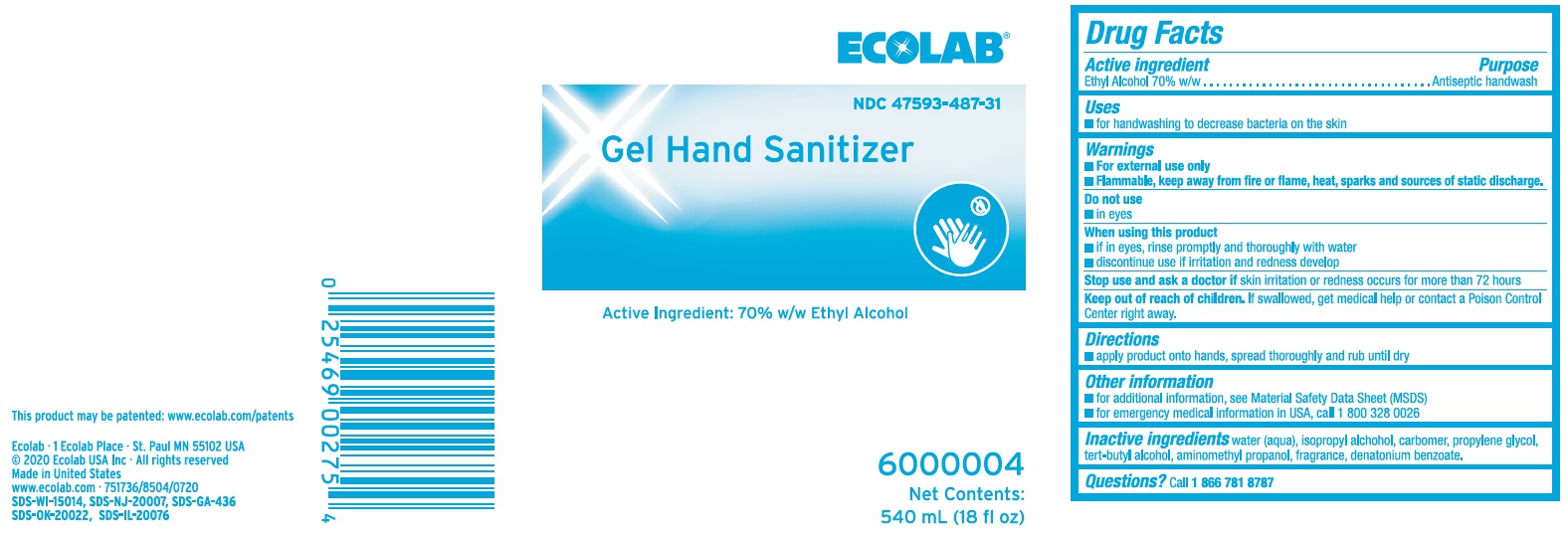 DRUG LABEL: Ecolab
NDC: 47593-487 | Form: SOLUTION
Manufacturer: Ecolab Inc.
Category: otc | Type: HUMAN OTC DRUG LABEL
Date: 20250731

ACTIVE INGREDIENTS: ALCOHOL 589.4 mg/1 mL
INACTIVE INGREDIENTS: WATER; ISOPROPYL ALCOHOL; CARBOMER INTERPOLYMER TYPE A (ALLYL SUCROSE CROSSLINKED); PROPYLENE GLYCOL; TERT-BUTYL ALCOHOL; AMINOMETHYLPROPANOL; DENATONIUM BENZOATE

Drug Facts

Active ingredient

Ethyl Alcohol 70% w/w

Purpose

Antiseptic handwash

Uses

- For handwashing to decrease bacteria on the skin

Warnings

- For external use only
- Flammable, keep away from fire or flame, heat, sparks and sources of static discharge

Do not use

- In eyes

When using this product

- If in eyes, rinse promptly and thoroughly with water
- Discontinue use if irritation and redness develop

Stop use and ask a doctor if

- Skin irritation or redness occurs for more than 72 hours

Keep out of reach of children. If swallowed, get medical help or contact a Poison Control Center right away.

Directions

- Apply product onto hands, spread thoroughly and rub until dry

Other information

- for additional information, see Material Safety Data Sheet (MSDS)
- for emergency medical information in USA, call 1 800 328 0026

INACTIVE INGREDIENT

Inactive ingredients water (aqua), isopropyl alcohol, carbomer, propylene glycol, tert-butyl alcohol, aminomethyl propanol, fragrance, denatonium benzoate.

Questions? call 1 866 781 8787

Principal display panel and representative label

ECOLAB®

NDC 47593-487-31

Gel Hand Sanitizer

Active Ingredient: 70% w/w Ethyl Alcohol

6000004

Net Contents:

540 mL (18 fl oz)

This product may be patented: www.ecolab.com/patents

Ecolab - 1 Eclab Place - St. Paul, MN 55102 USA

(c) 2020 Ecolab USA Inc - All rights reserved

Made in United States

www.ecolab.com - 751736/8504/0720

SDS-WI-15014, SDS-NJ-20007, SDS-GA-436

SDS-OK-20022, SDS-IL-20076